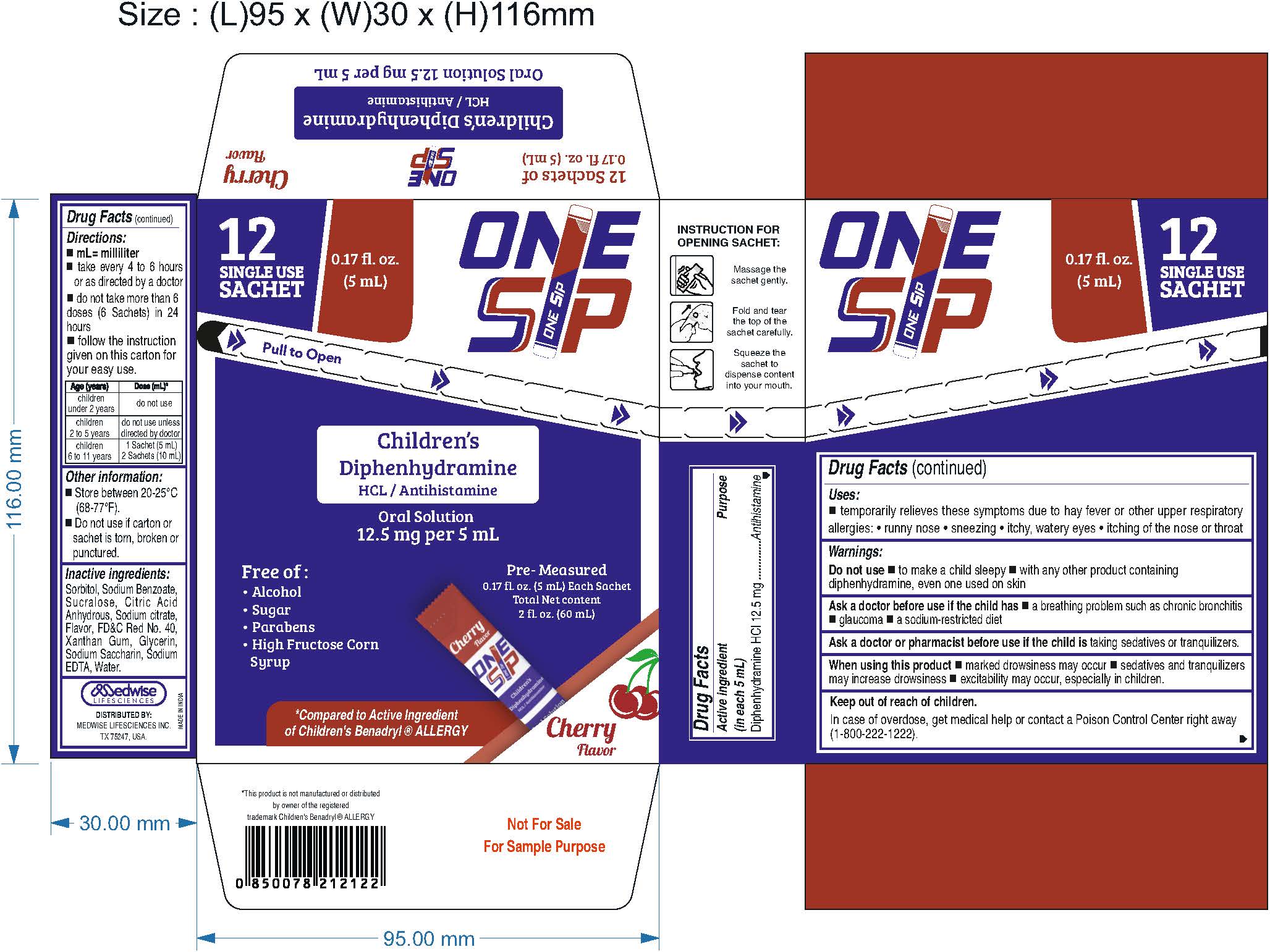 DRUG LABEL: OneSsip Diphenhydramine HCl 12.5 mg/ 5 mL Oral Solution (Cherry)
NDC: 87078-421 | Form: SOLUTION
Manufacturer: MEDWISE LIFESCIENCES INC.
Category: otc | Type: HUMAN OTC DRUG LABEL
Date: 20251017

ACTIVE INGREDIENTS: DIPHENHYDRAMINE HYDROCHLORIDE 12.5 mg/5 mL
INACTIVE INGREDIENTS: EDETATE DISODIUM; ANHYDROUS CITRIC ACID; SUCRALOSE; SODIUM SACCHARIN; WATER; SODIUM BENZOATE; SORBITOL SOLUTION; SODIUM CITRATE; XANTHAN GUM; GLYCERIN; FD&C RED NO. 40

OneSsip Diphenhydramine HCl 12.5 mg / 5 mL Oral Solution for Children (Cherry)
Drug Facts

Active ingredient (in each 5 mL)

Diphenhydramine HCl 12.5 mg

Purpose

Antihistamine

Uses

- temporarily relieves these symptoms due to hay fever or other upper respiratory allergies:
  - runny nose
  - sneezing
  - itchy, watery eyes
  - itching of the nose or throat

Warnings

Do not use

- to make a child sleepy
- with any other product containing diphenhydramine, even one used on skin

Ask a doctor before use if the child has

- a breathing problem such as chronic bronchitis
- glaucoma
- a sodium-restricted diet

Ask a doctor or pharmacist before use if the child istaking sedatives or tranquilizers.

When using this product

- marked drowsiness may occur
- sedatives and tranquilizers may increase drowsiness
- excitability may occur, especially in children

Keep out of reach of children.

In case of overdose, get medical help or contact a Poison Control Center right away. (1-800-222-1222)

Directions

- mL = milliliter
- take every 4 to 6 hours or as directed by a doctor
- do not take more than 6 doses (6 sachets) in 24 hours
- follow the instruction given on this carton for your easy use

Age (years) | Dose (mL)
Children under 2 Years | do not use
Children 2 to 5 Years | do not use unless directed by doctor
Children 6 to 11 Years | 1 Sachet (5 mL) to 2 Sachets (10 mL)

Other Information

- store between 20-25°C (68-77°F)
- Do not use if carton or sachet is torn, broken or punctured.

Inactive Ingredients

Sorbitol, sodium benzoate, sucralose, citric acid anhydrous, sodium citrate, flavor, FD&C Red No. 40, xanthan gum, glycerin, sodium saccharin, sodium EDTA, water.

Question or comments?

call 1-516-675-8915

RECENT MAJOR CHANGES

Addition of picture